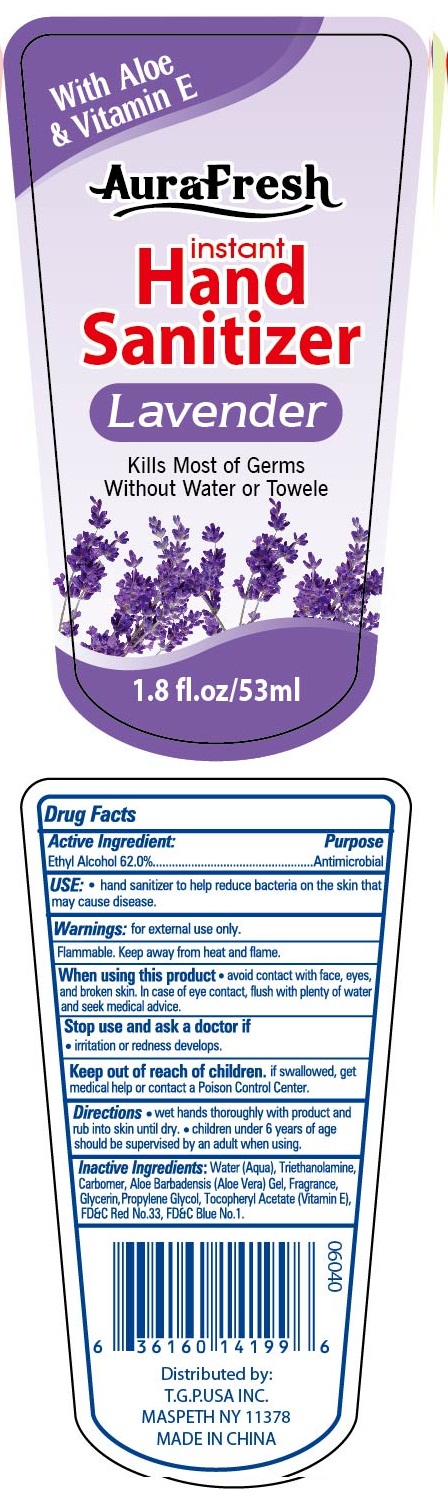 DRUG LABEL: aurafresh instant hand sanitizer with aloe and vitamin e
NDC: 40104-286 | Form: GEL
Manufacturer: Ningbo Pulisi Daily Chemical Products Co., Ltd.
Category: otc | Type: HUMAN OTC DRUG LABEL
Date: 20170810

ACTIVE INGREDIENTS: alcohol 62 mL/100 mL
INACTIVE INGREDIENTS: WATER; PROPYLENE GLYCOL; ALOE VERA LEAF; FD&C BLUE NO. 1; GLYCERIN; .ALPHA.-TOCOPHEROL ACETATE, D-; TROLAMINE

Drug facts

Active ingredient Purpose

Ethyl Alcohol 62% ... Antiseptic

PURPOSE

Hand sanitizer to help decrease bacteria on the skin.

KEEP OUT OF REACH OF CHILDREN

If swallowed, get medical help or contact local poison control center right away.

Children under 6 years of age should be supervised by an adult when using.

when using this product, avoid contact with face, eyes and broken skin. In case of eye contact, flush with plenty of water and seek medical advice.

WARNINGS

For external use only.
Flammable. Keep away from hear or flame.

Stop using and ask a doctor, if irritation and redness develops.

DOSAGE AND ADMINISTRATION

wet hands thoroughly with product and rub into skin until dry.

INACTIVE INGREDIENT

Water, Carbomer, Glycerin, Propylene Glycol, Triethanolamine, Aloe Barbadensis Leaf Juice, Tocopheryl Acetate, Fragrance, red 33, blue 1